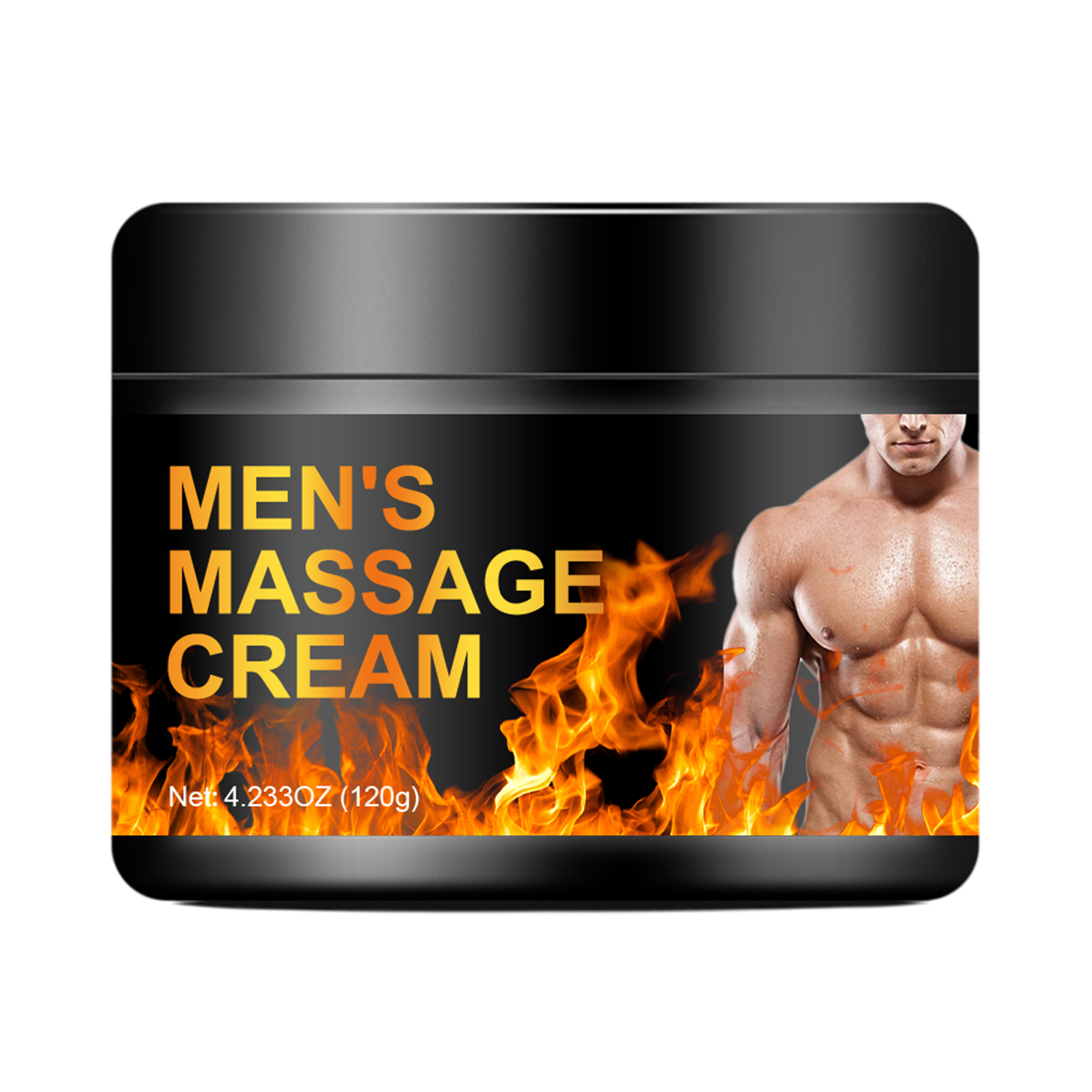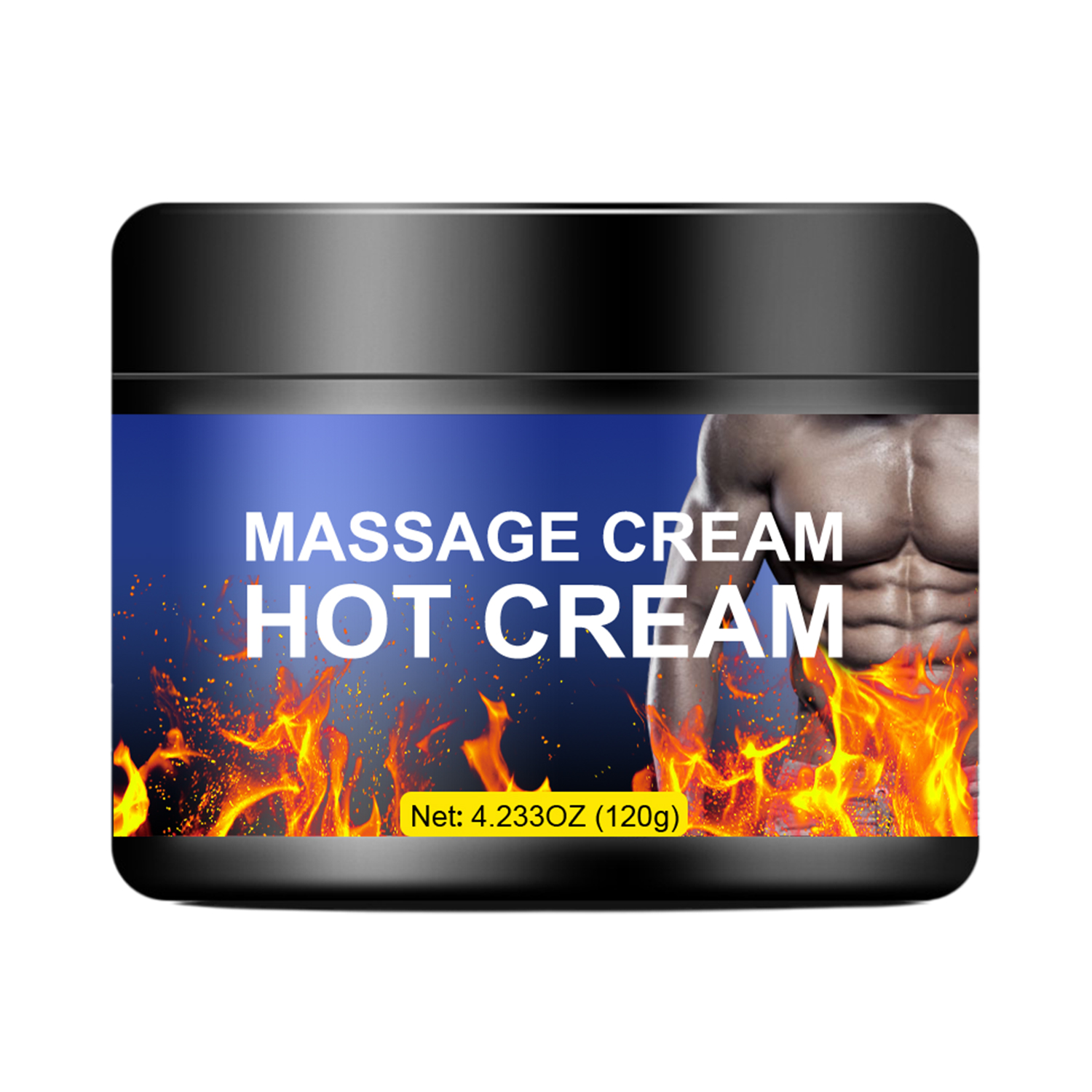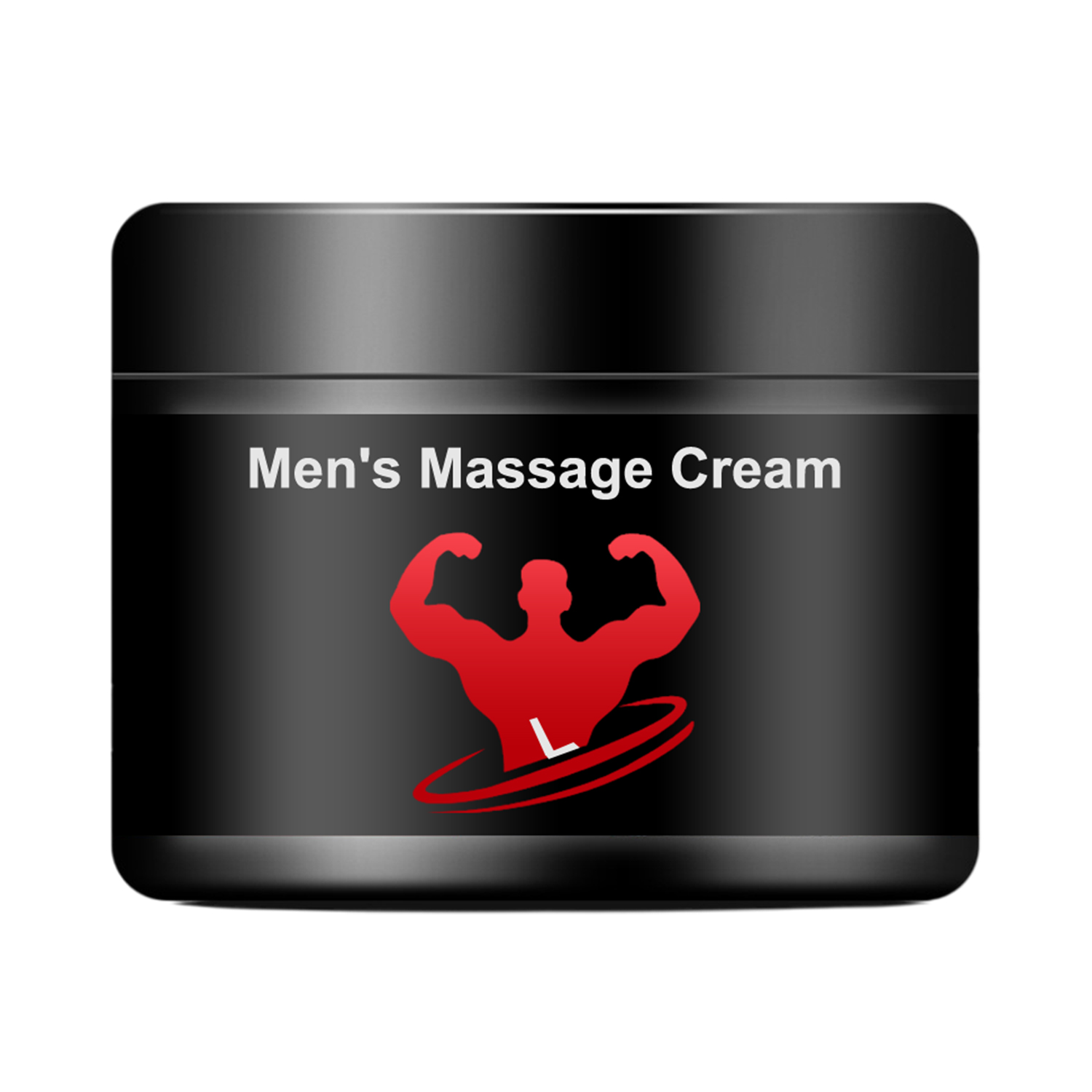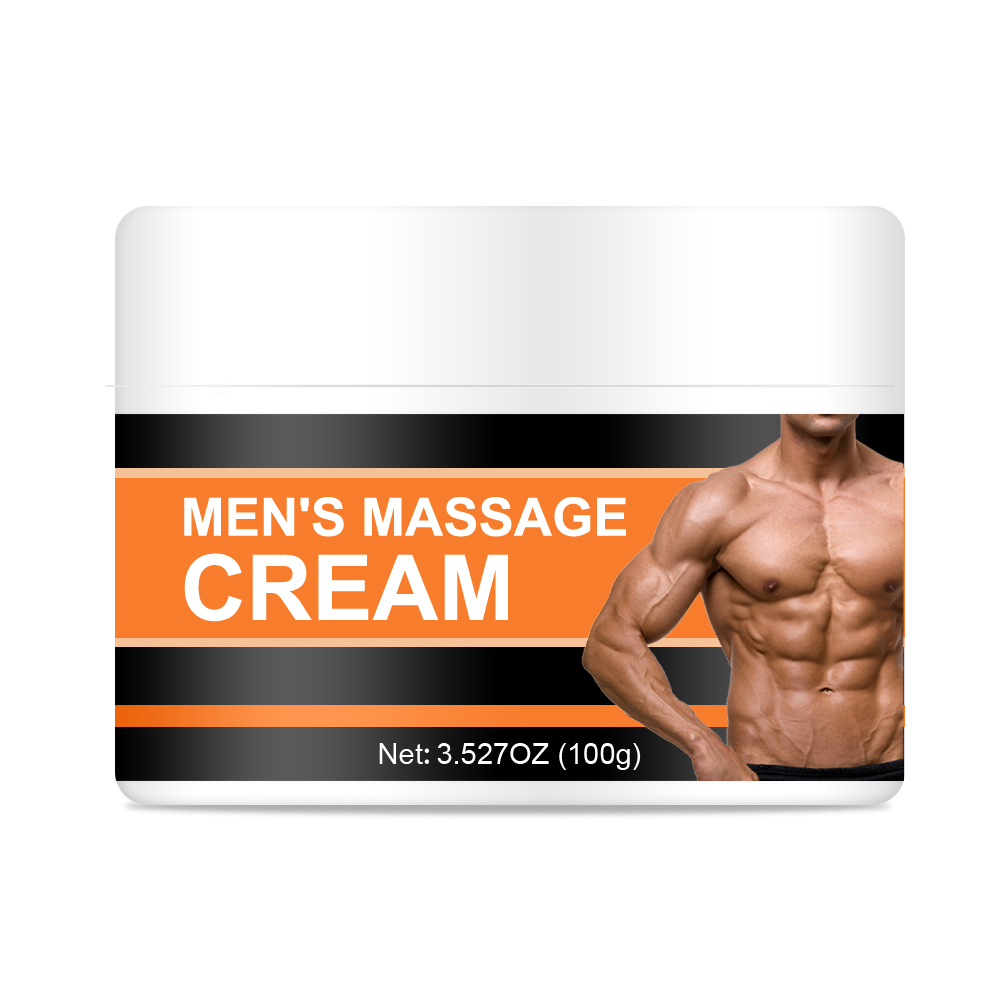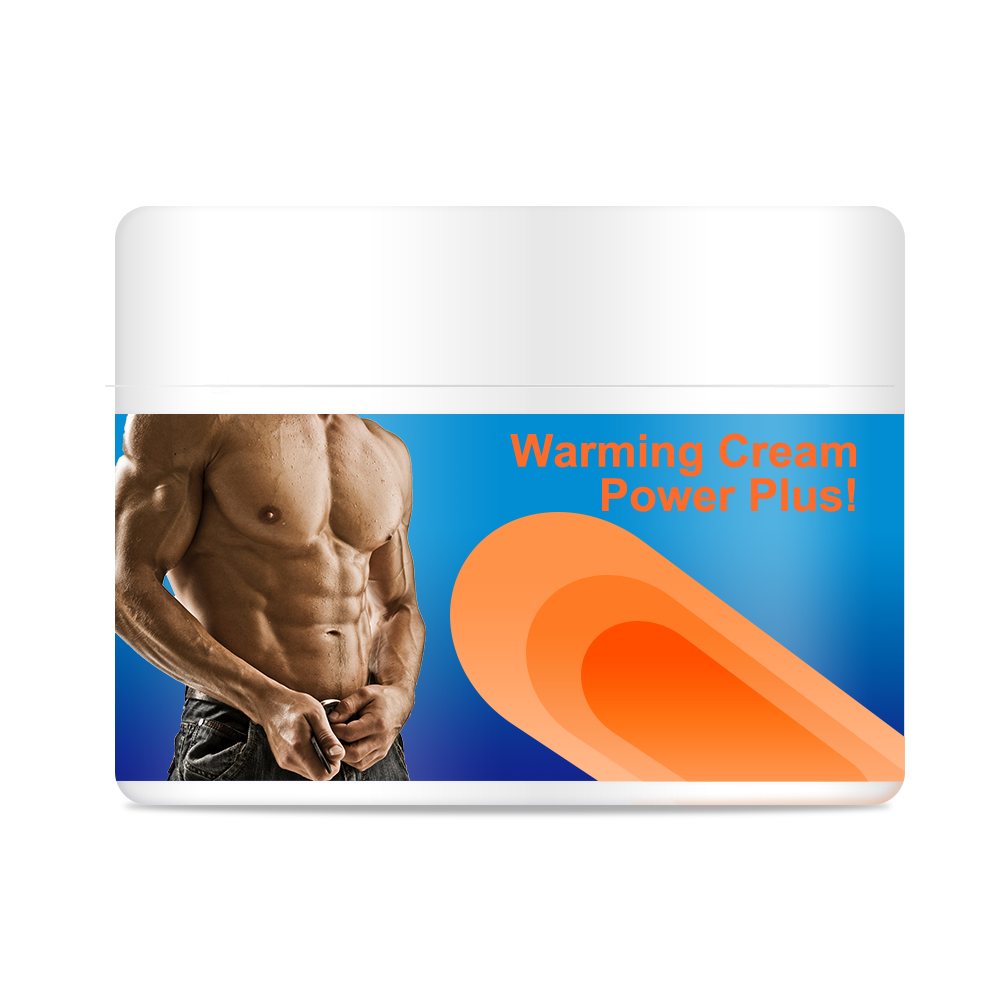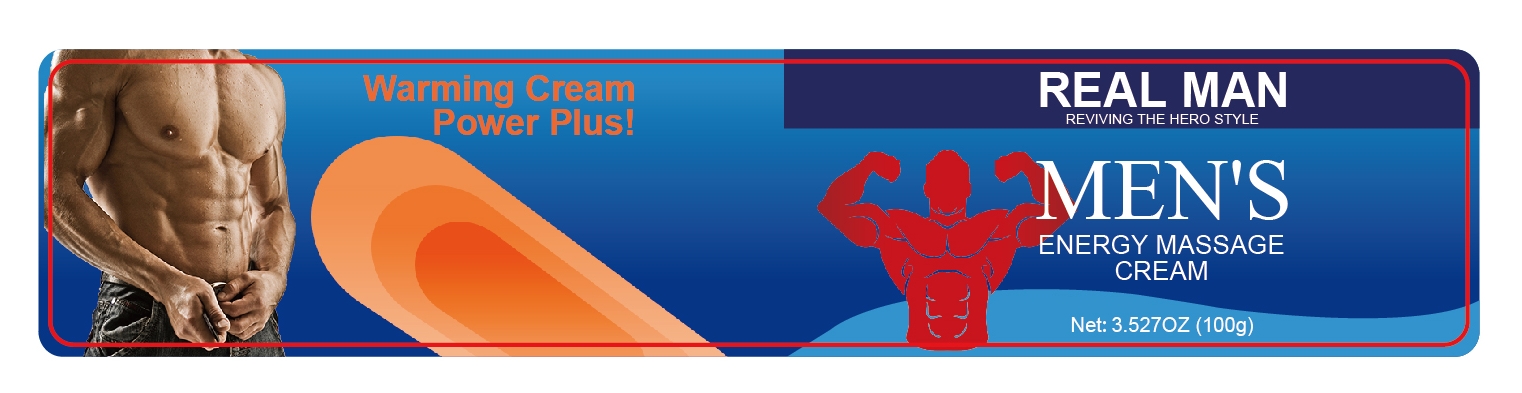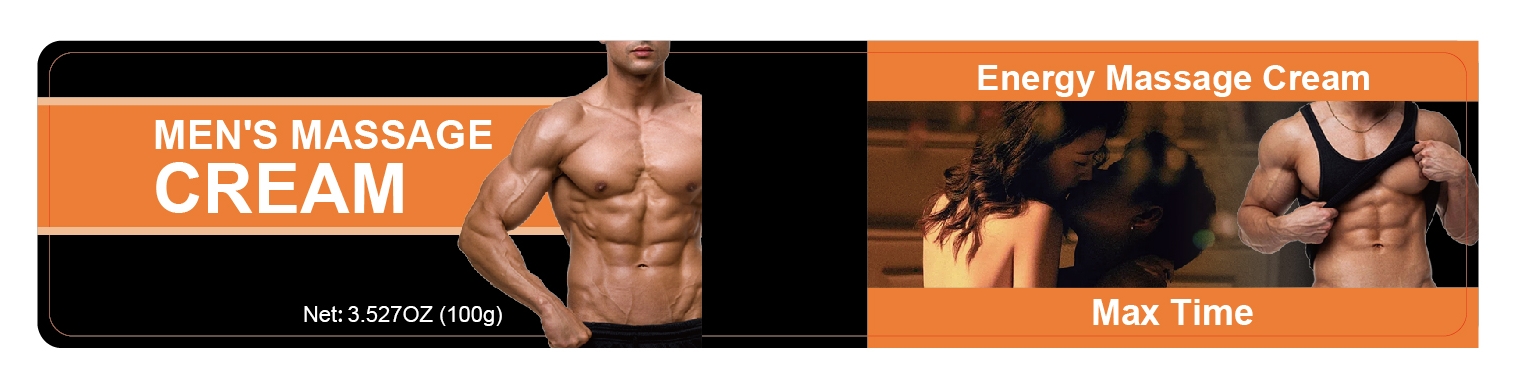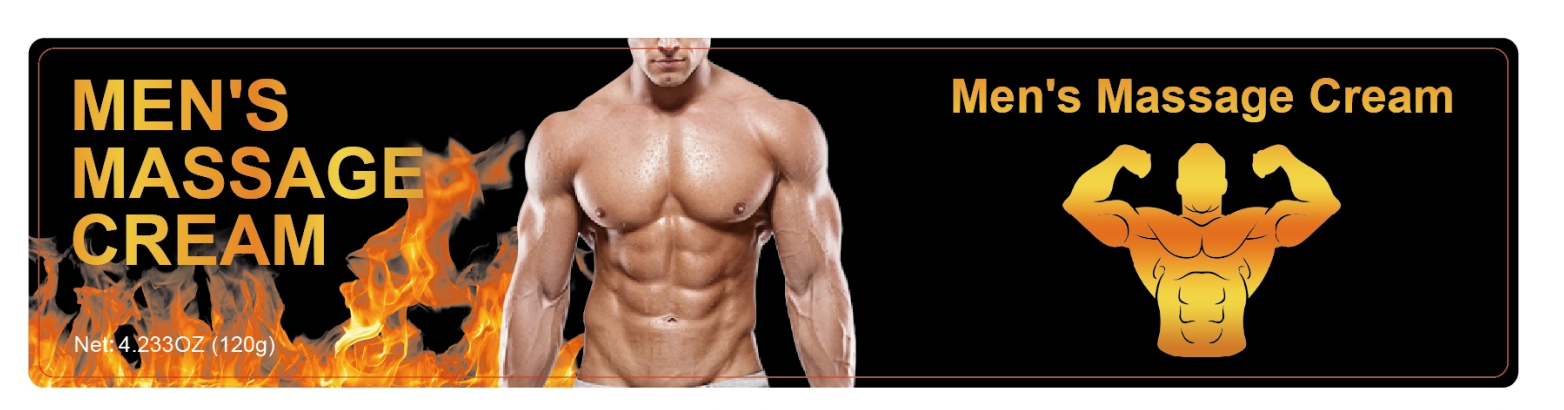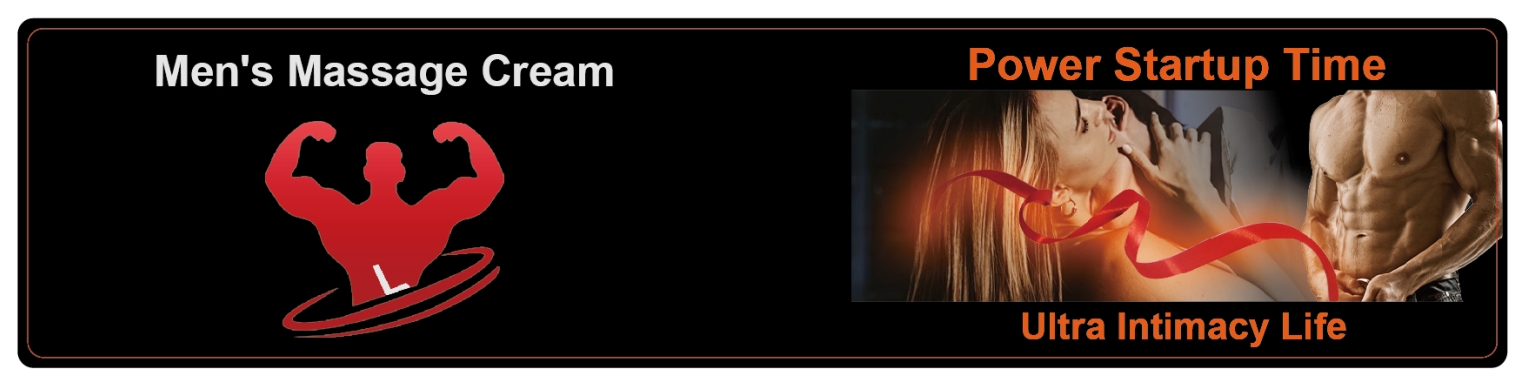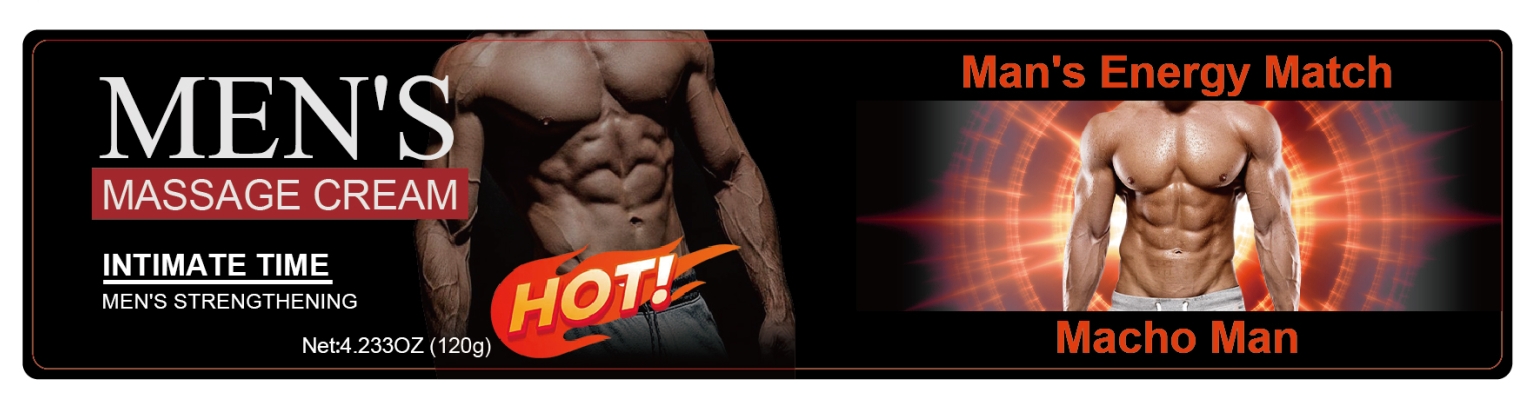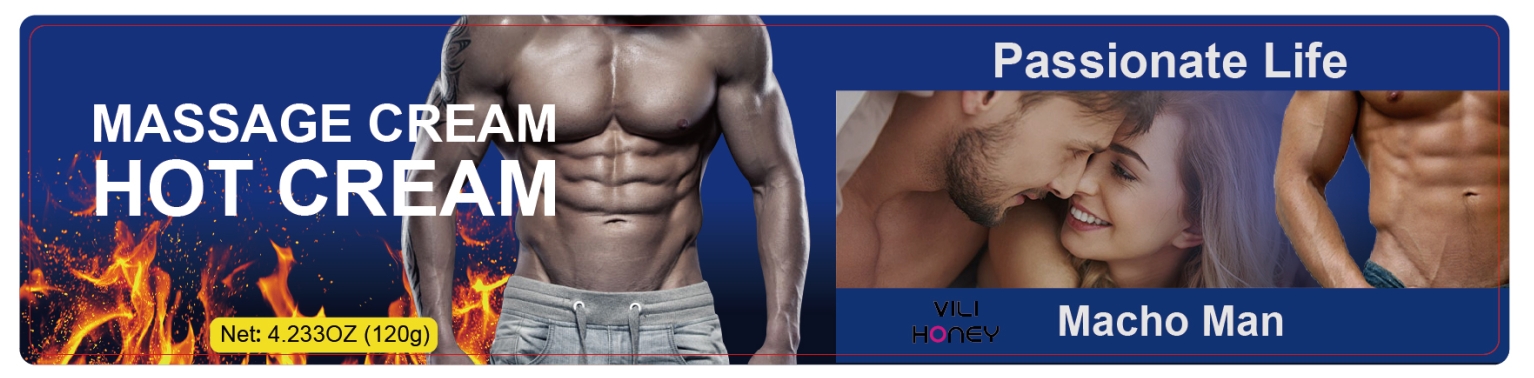 DRUG LABEL: Mens Massage Cream
NDC: 84025-044 | Form: CREAM
Manufacturer: Guangzhou Yanxi Biotechnology Co., Ltd
Category: otc | Type: HUMAN OTC DRUG LABEL
Date: 20240624

ACTIVE INGREDIENTS: GLYCERIN 5 mg/120 g; PANTHENOL 3 mg/120 g
INACTIVE INGREDIENTS: WATER

DOSAGE AND ADMINISTRATION

Apply to affected area twice per day on cleansed skin. Use continuously for 2-3 weeks for best results.

WARNINGS

Keep out of Children

INACTIVE INGREDIENT

aqua

INDICATIONS AND USAGE

for men use

Keep out of Children

PURPOSE

for men use